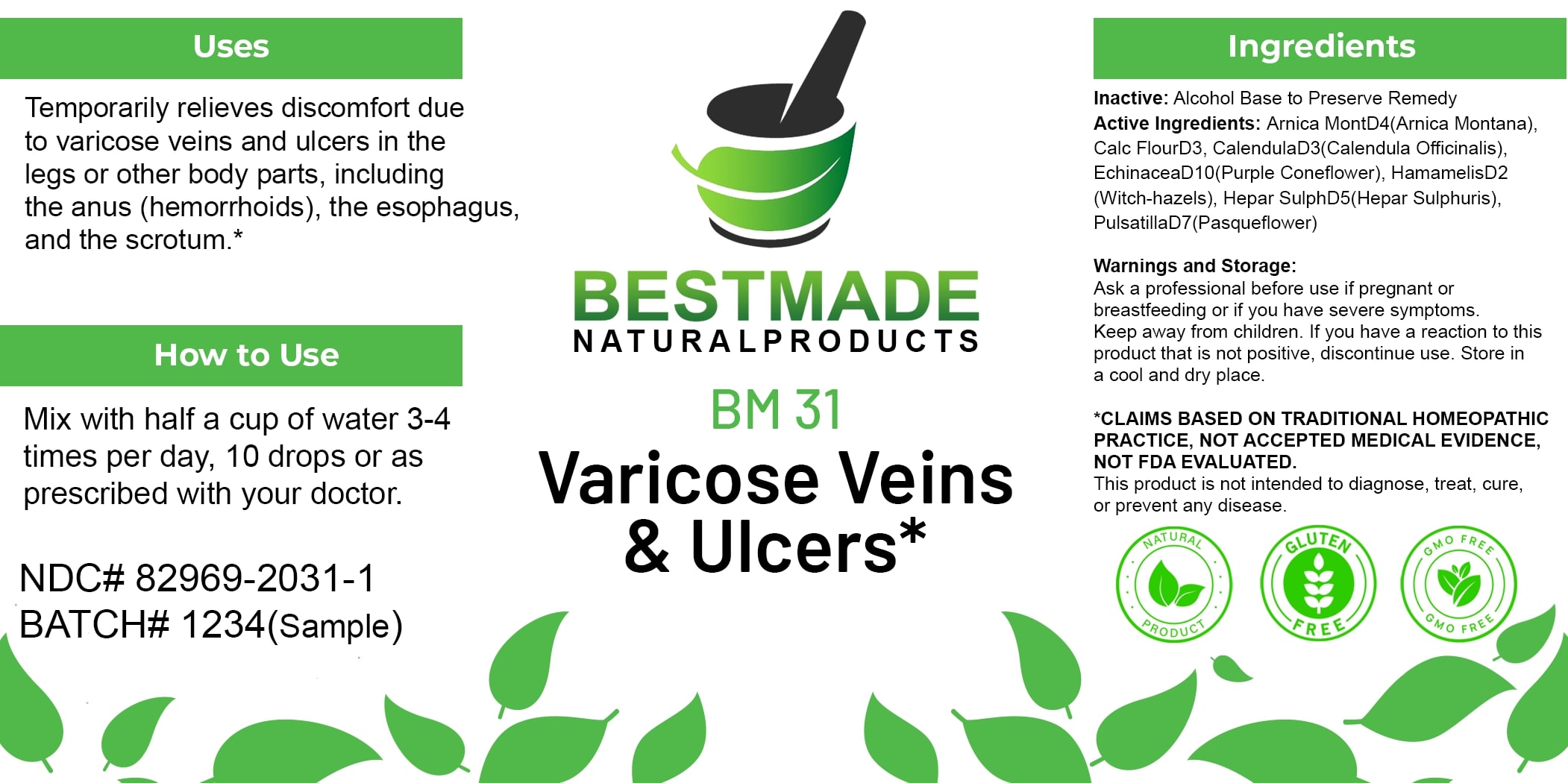 DRUG LABEL: Bestmade Natural Products BM31
NDC: 82969-2031 | Form: LIQUID
Manufacturer: Bestmade Natural Products
Category: homeopathic | Type: HUMAN OTC DRUG LABEL
Date: 20250123

ACTIVE INGREDIENTS: CALENDULA OFFICINALIS FLOWER 30 [hp_C]/30 [hp_C]; CALCIUM SULFIDE 30 [hp_C]/30 [hp_C]; ARNICA MONTANA 30 [hp_C]/30 [hp_C]; HAMAMELIS VIRGINIANA ROOT BARK/STEM BARK 30 [hp_C]/30 [hp_C]; ECHINACEA ANGUSTIFOLIA 30 [hp_C]/30 [hp_C]; CALCIUM FLUORIDE 30 [hp_C]/30 [hp_C]; PULSATILLA PRATENSIS 30 [hp_C]/30 [hp_C]
INACTIVE INGREDIENTS: ALCOHOL 30 [hp_C]/30 [hp_C]

BM31

DOSAGE AND ADMINISTRATION

How to Use

Mix with half a cup of water 3-4 times per day, 10 drops or as prescribed with your doctor.

INACTIVE INGREDIENT

Ingredients

Inactive: Alcohol Base to Preserve Remedy

Uses

Temporarily relieves discomfort due to varicose veins and ulcers in the legs or other body parts, including the anus (hemorrhoids), the esophagus, and the scrotum.*

*CLAIMS BASED ON TRADITIONAL HOMEOPATHIC PRACTICE, NOT ACCEPTED MEDICAL EVIDENCE, NOT FDA EVALUATED.

This product is not intended to diagnose, treat, cure, or prevent any disease.

Uses

Temporarily relieves discomfort due to varicose veins and ulcers in the legs or other body parts, including the anus (hemorrhoids), the esophagus, and the scrotum.*

*CLAIMS BASED ON TRADITIONAL HOMEOPATHIC PRACTICE, NOT ACCEPTED MEDICAL EVIDENCE, NOT FDA EVALUATED.

This product is not intended to diagnose, treat, cure, or prevent any disease.

ACTIVE INGREDIENT

Active Ingredients: Arnica Mont D4 (Arnica Montana), Calc Flour D3, Calendula D3 (Calendula Officinalis), Echinacea D10 (Purple Coneflower), Hamamelis D2 (Witch-hazels), Hepar Sulph D5 (Hepar Sulphuris), Pulsatilla D7 (Pasqueflower)

KEEP OUT OF REACH OF CHILDREN

Warnings and Storage:

Ask a professional before use if pregnant or breastfeeding or if you have severe symptoms. Keep away from children. If you have a reaction to this product that is not positive, discontinue use. Store in a cool and dry place.

Warnings and Storage:

Ask a professional before use if pregnant or breastfeeding or if you have severe symptoms. Keep away from children. If you have a reaction to this product that is not positive, discontinue use. Store in a cool and dry place.

*CLAIMS BASED ON TRADITIONAL HOMEOPATHIC PRACTICE, NOT ACCEPTED MEDICAL EVIDENCE, NOT FDA EVALUATED.

This product is not intended to diagnose, treat, cure, or prevent any disease.

Entire package label